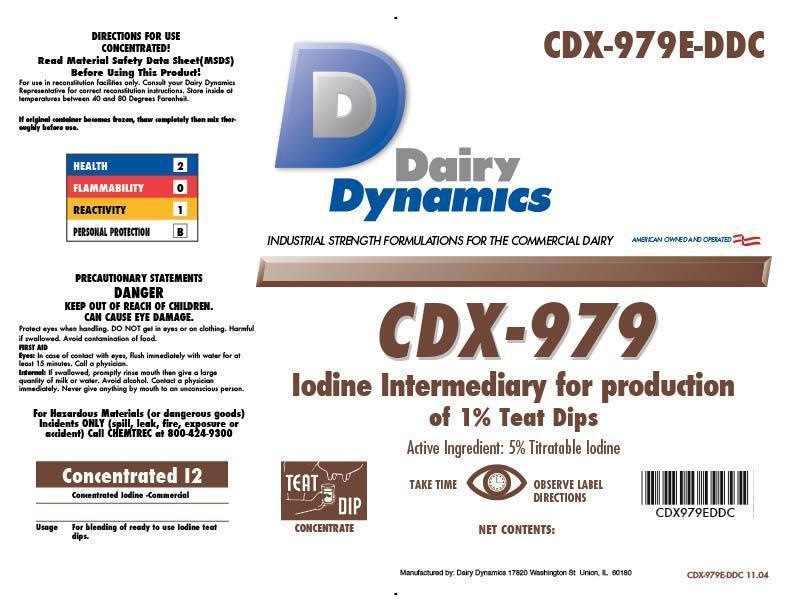 DRUG LABEL: CDX-979
NDC: 67351-979 | Form: LIQUID
Manufacturer: Dairy Dynamics L.L.C.
Category: animal | Type: OTC ANIMAL DRUG LABEL
Date: 20141118

ACTIVE INGREDIENTS: IODINE 50 g/1 L

CDX-979

PRECAUTIONS

Read Material Safety Data Sheet (MSDS) Before Using This Product!

For use in reconstitution facilities only. Consult your Dairy Dynamics Representative for correct reconstitution instructions. Store inside at temperatures 40 and 80 Degrees Fahrenheit.

If original container becomes frozen, thaw completely then mix thoroughly before use.

PRECAUTIONARY STATEMENTS

DANGER

KEEP OUT OF REACH OF CHILDREN. CAN CAUSE EYE DAMAGE.

Protect eyes when handling. DO NOT get in eyes or on clothing. Harmful if swallowed. Avoid contamination of food.

FIRST AID

Eyes: In case of contact with eyes, flush immediately with water for at least 15 minutes. Call a physician.

Internal: If swallowed, promptly rinse mouth, then give a large quantity of milk or water. Avoid alcohol. Contact a physician immediately. Never give anything by mouth to an unconscious person.

For Hazardous Materials (or dangerous goods) Incidents ONLY (spill, leak, fire, exposure or accident) Call CHEMTREC at 800-424-9300.

HEALTH - 2

FLAMMABILITY - 0

REACTIVITY - 1

PERSONAL PROTECTION - B

INDICATIONS AND USAGE

Iodine Intermediary for production of 1% Teat Dips

For use in reconstitution facilities only.

Concentrated Iodine Solution